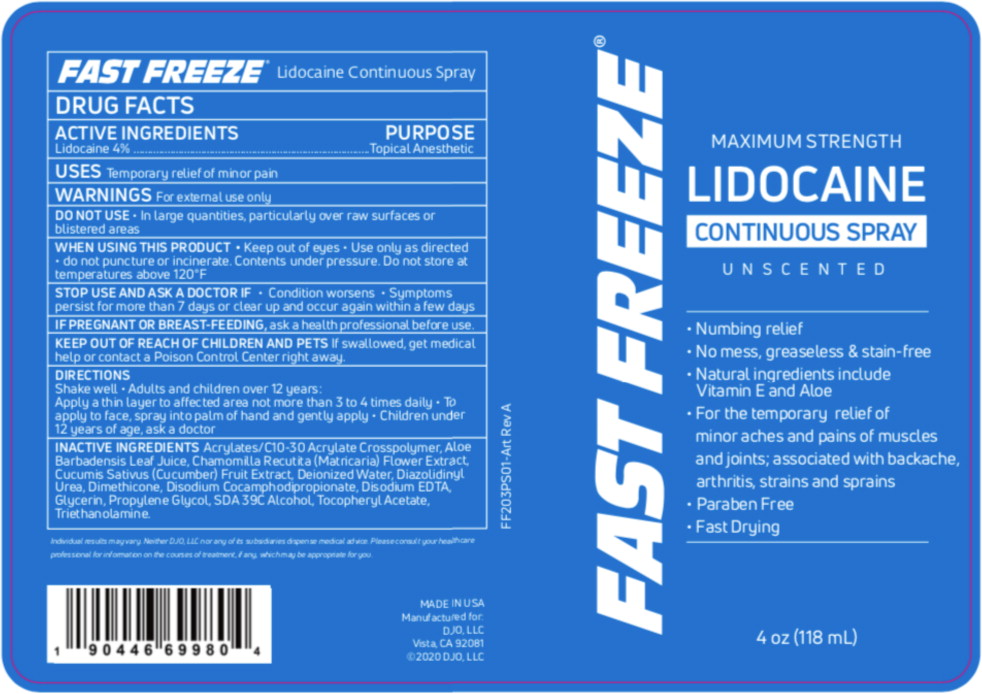 DRUG LABEL: Fast Freeze Lidocaine
NDC: 66902-225 | Form: SPRAY
Manufacturer: Natural Essentials, Inc.
Category: otc | Type: HUMAN OTC DRUG LABEL
Date: 20241004

ACTIVE INGREDIENTS: LIDOCAINE 40 mg/1 mL
INACTIVE INGREDIENTS: CARBOMER COPOLYMER TYPE A (ALLYL PENTAERYTHRITOL CROSSLINKED); ALOE VERA LEAF; MATRICARIA CHAMOMILLA FLOWERING TOP; CUCUMBER; WATER; DIAZOLIDINYL UREA; DIMETHICONE; DISODIUM COCOAMPHODIPROPIONATE; EDETATE DISODIUM; GLYCERIN; PROPYLENE GLYCOL; ALCOHOL; .ALPHA.-TOCOPHEROL ACETATE; TROLAMINE

DRUG FACTS

ACTIVE INGREDIENTS

Lidocaine 4%

PURPOSE

Topical Anesthetic

USES

Temporary relief of minor pain

WARNINGS

For external use only

DO NOT USE

- In large quantities, particularly over raw surfaces or blistered areas

WHEN USING THIS PRODUCT

- Keep out of eyes
- Use only as directed
- do not puncture or incinerate. Contents under pressure. Do not store at temperatures above 120°F

STOP USE AND ASK A DOCTOR IF

- Condition worsens
- Symptoms persist for more than 7 days or clear up and occur again within a few days

PREGNANCY OR BREAST FEEDING

IF PREGNANT OR BREAST-FEEDING, ask a health professional before use.

KEEP OUT OF REACH OF CHILDREN AND PETSIf swallowed, get medical help or contact a Poison Control Center right away

DIRECTIONS

Shake well

- Adults and children over 12 years:

Apply a thin layer to affected area not more than 3 to 4 times daily

- To apply to face, spray into palm of hand and gently apply
- Children under 12 years of age, ask a doctor

INACTIVE INGREDIENTS

Acrylates/C10-30 Acrylate Crosspolymer, Aloe Barbadensis Leaf Juice, Chamomilla Recutita (Matricaria) Flower Extract, Cucumis Sativus (Cucumber) Fruit Extract, Deionized Water, Diazolidinyl Urea. Dimethicone, Disodium Cocamphodipropionate. Disodium EDTA, Glycerin. Propylene Glycol, SDA 39C Alcohol, Tocopheryl Acetate, Triethanolamine.

Principal Display Panel – 118 mL Can Label

FAST FREEZE®

MAXIMUM STRENGTH
LIDOCAINE
CONTINUOUS SPRAY

UNSCENTED

- Numbing relief
- No mess, greaseless & stain-free
- Natural ingredients include
  Vitamin E and Aloe
- For the temporary relief of
  minor aches and pains of muscles
  and joints; associated with backache,
  arthritis, strains and sprains
- Paraben Free
- Fast Drying

3 oz (89 mL)